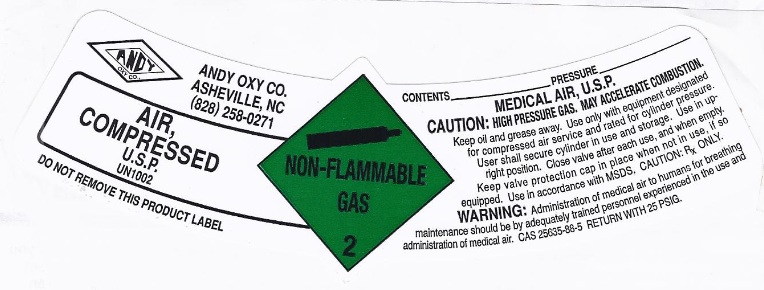 DRUG LABEL: Air
NDC: 50063-003 | Form: GAS
Manufacturer: Andy-Oxy Co., Inc.
Category: prescription | Type: HUMAN PRESCRIPTION DRUG LABEL
Date: 20121229

ACTIVE INGREDIENTS: Air 1000 mL/1 L

Air

PACKAGE LABEL

ANDY OXY CO. ASHEVILLE, NC (828) 258-0271 AIR, COMPRESSED U.S.P. UN1002 DO NOT REMOVE THIS PRODUCT LABEL. NON-FLAMMABLE GAS 2 CONTENTS PRESSURE MEDICAL AIR, U.S.P. CAUTION: HIGH PRESSURE GAS. MAY ACCELERATE COMBUSTION. Keep oil and grease away. Use only with equipment designated for compressed air service and rated for cylinder pressure. User shall secure cylinder in use and storage. Use in upright position. Close valve after each use, and when empty. Keep valve protection cap in place when not in use, if so equipped. Use in accordance with MSDS. CAUTION: Rx ONLY. WARNING: Administration of medical air to humans for breathing maintenance should be by adequately trained personnel experienced in the use and administration of medical air. CAS 25635-88-5 RETURN WITH 25 PSIG.